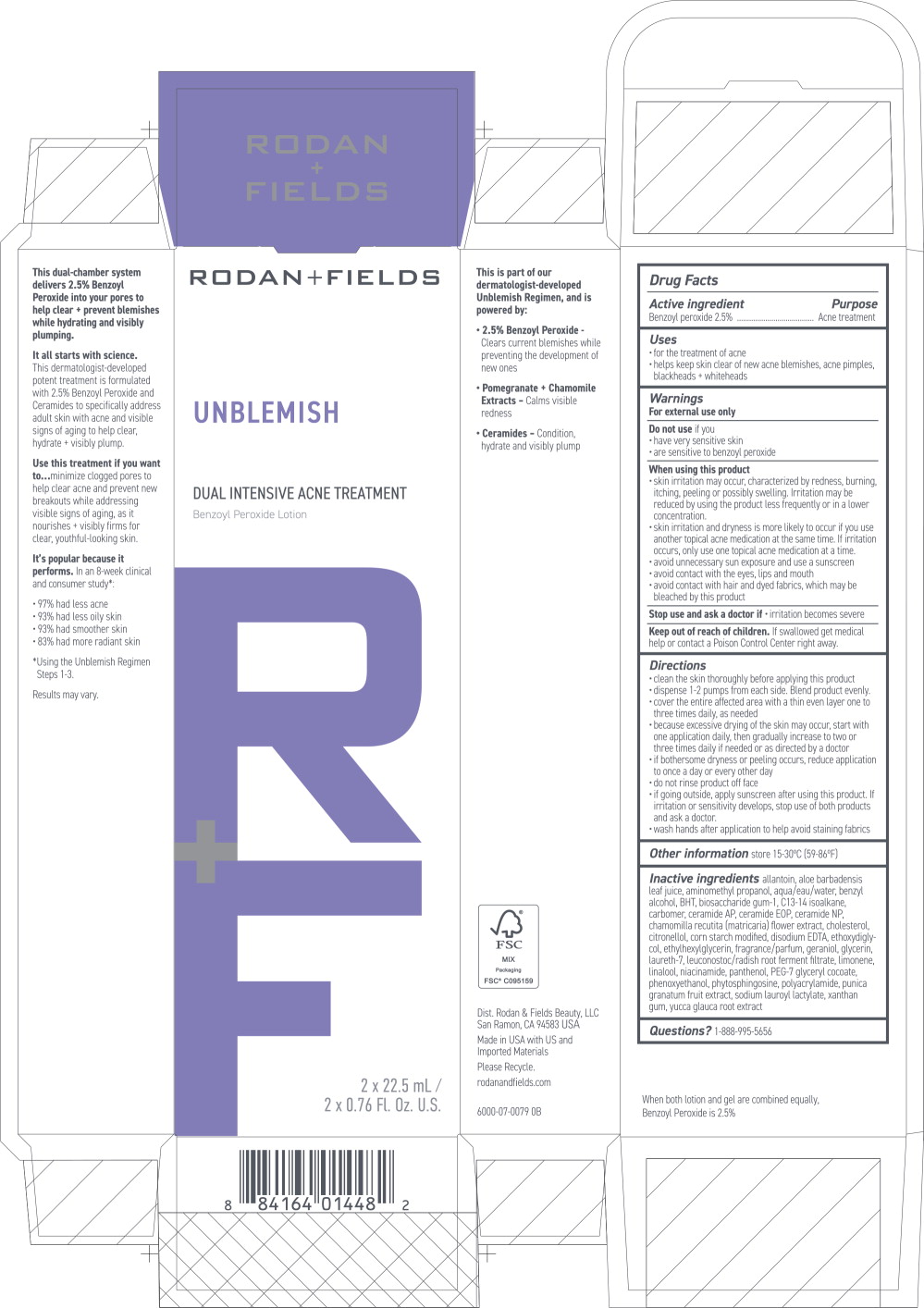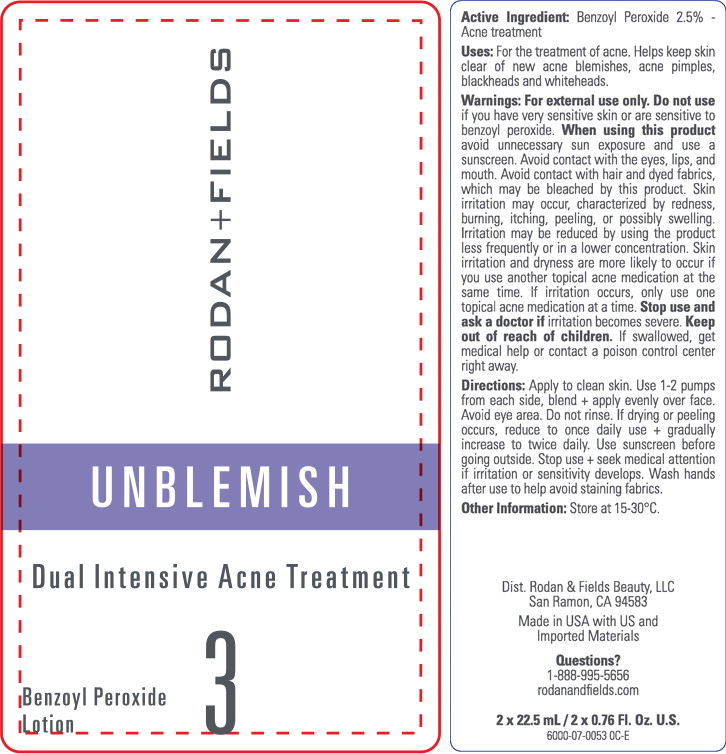 DRUG LABEL: UNBLEMISH Dual Intensive Acne Treatment
NDC: 14222-2120 | Form: LOTION
Manufacturer: Rodan & Fields
Category: otc | Type: HUMAN OTC DRUG LABEL
Date: 20250924

ACTIVE INGREDIENTS: BENZOYL PEROXIDE 0.025 g/1 mL
INACTIVE INGREDIENTS: WATER; DIETHYLENE GLYCOL MONOETHYL ETHER; GLYCERIN; POLYACRYLAMIDE (10000 MW); .BETA.-CITRONELLOL, (R)-; ALLANTOIN; ALOE VERA LEAF; AMINOMETHYLPROPANOL; BENZYL ALCOHOL; BIOSACCHARIDE GUM-1; BUTYLATED HYDROXYTOLUENE; C13-14 ISOPARAFFIN; CARBOXYPOLYMETHYLENE; CERAMIDE 1; CERAMIDE AP; CERAMIDE NP; CHOLESTEROL; EDETATE DISODIUM ANHYDROUS; ETHYLHEXYLGLYCERIN; GERANIOL; LAURETH-7; LEUCONOSTOC/RADISH ROOT FERMENT FILTRATE; LIMONENE, (+)-; LINALOOL, (+/-)-; MATRICARIA CHAMOMILLA FLOWERING TOP; NIACINAMIDE; PANTHENOL; PEG-7 GLYCERYL COCOATE; PHENOXYETHANOL; PHYTOSPHINGOSINE; POMEGRANATE; SODIUM LAUROYL LACTYLATE; STARCH, CORN; XANTHAN GUM; YUCCA GLAUCA ROOT

Drug Facts

Active ingredient

Benzoyl peroxide 2.5%

Purpose

Acne treatment

Uses

- for the treatment of acne
- helps keep skin clear of new acne blemishes, acne pimples, blackheads + whiteheads

Warnings

For external use only

Do not use if you

- have very sensitive skin
- are sensitive to benzoyl peroxide

When using this product

- skin irritation may occur, characterized by redness, burning, itching, peeling or possibly swelling. Irritation may be reduced by using the product less frequently or in a lower concentration.
- skin irritation and dryness is more likely to occur if you use another topical acne medication at the same time. If irritation occurs, only use one topical acne medication at a time.
- avoid unnecessary sun exposure and use a sunscreen
- avoid contact with the eyes, lips and mouth
- avoid contact with hair and dyed fabrics, which may be bleached by this product

Stop use and ask a doctor if

- irritation becomes severe

Keep out of reach of children. If swallowed get medical help or contact a Poison Control Center right away.

Directions

- clean the skin thoroughly before applying this product
- dispense 1-2 pumps from each side. Blend product evenly.
- cover the entire affected area with a thin even layer one to three times daily, as needed
- because excessive drying of the skin may occur, start with one application daily, then gradually increase to two or three times daily if needed or as directed by a doctor
- if bothersome dryness or peeling occurs, reduce application to once a day or every other day
- do not rinse product off face
- if going outside, apply sunscreen after using this product. If irritation or sensitivity develops, stop use of both products and ask a doctor.
- wash hands after application to help avoid staining fabrics

Other information store 15-30°C (59-86°F)

INACTIVE INGREDIENT

Inactive ingredients allantoin, aloe barbadensis leaf juice, aminomethyl propanol, aqua/eau/water, benzyl alcohol, BHT, biosaccharide gum-1, C13-14 isoalkane, carbomer, ceramide AP, ceramide EOP, ceramide NP, chamomilla recutita (matricaria) flower extract, cholesterol, citronellol, corn starch modified, disodium EDTA, ethoxydiglycol, ethylhexylglycerin, fragrance/parfum, geraniol, glycerin, laureth-7, leuconostoc/radish root ferment filtrate, limonene, linalool, niacinamide, panthenol, PEG-7 glyceryl cocoate, phenoxyethanol, phytosphingosine, polyacrylamide, punica granatum fruit extract, sodium lauroyl lactylate, xanthan gum, yucca glauca root extract

Questions? 1-888-995-5656

Principal Display Panel - 45mL / 1.5 Fl. Oz. Carton Label

RODAN+FIELDS

UNBLEMISH

DUAL INTENSIVE ACNE TREATMENT
Benzoyl Peroxide Lotion

R+F

2 x 22.5 mL /
2 x 0.76 Fl. Oz. U.S.

Principal Display Panel - 45mL / 1.5 Fl. Oz. Tube Label

RODAN+FIELDS

UNBLEMISH

Dual Intensive Acne Treatment

Benzoyl Peroxide
Lotion

3